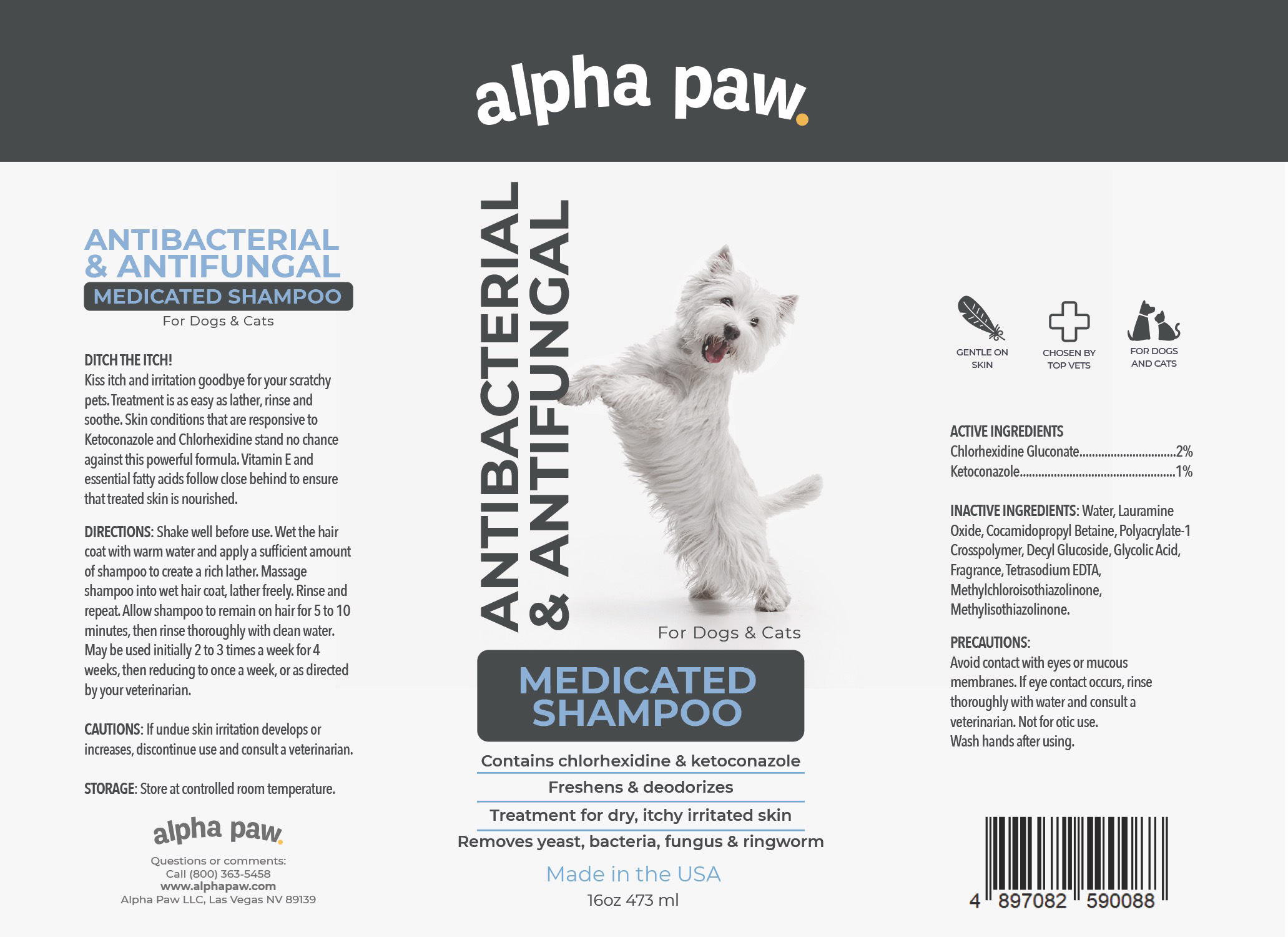 DRUG LABEL: ANTIBACTERIAL ANTIFUNGAL MEDICATED
NDC: 86175-002 | Form: SHAMPOO
Manufacturer: Alpha Paw Inc
Category: animal | Type: OTC ANIMAL DRUG LABEL
Date: 20230330

ACTIVE INGREDIENTS: CHLORHEXIDINE GLUCONATE 2 g/100 mL; KETOCONAZOLE 1 g/100 mL
INACTIVE INGREDIENTS: WATER; LAURAMINE OXIDE; COCAMIDOPROPYL BETAINE; POLYACRYLATE-1 CROSSPOLYMER; DECYL GLUCOSIDE; EDETATE SODIUM; METHYLCHLOROISOTHIAZOLINONE; METHYLISOTHIAZOLINONE

ANTIBACTERIAL & ANTIFUNGAL MEDICATED SHAMPOO

ACTIVE INGREDIENTS

Chlorhexidine Gluconate...............................2%
Ketoconazole..................................................1%

PURPOSE

ANTIBACTERIAL & ANTIFUNGAL MEDICATED SHAMPOO For Dogs & Cats

DITCH THE ITCH!

Kiss itch and irritation goodbye for your scratchy pets. Treatment is as easy as lather, rinse and soothe. Skin conditions that are responsive to Ketoconazole and Chlorhexidine stand no chance against this powerful formula. Vitamin E and essential fatty acids follow close behind to ensure that treated skin is nourished.

INACTIVE INGREDIENTS

Water, Lauramine Oxide, Cocamidopropyl Betaine, Polyacrylate-1 Crosspolymer, Decyl Glucoside, Glycolic Acid, Fragrance, Tetrasodium EDTA, Methylchloroisothiazolinone, Methylisothiazolinone.

PRECAUTIONS

Avoid contact with eyes or mucous membranes. If eye contact occurs, rinse thoroughly with water and consult a veterinarian. Not for otic use. Wash hands after using.

DIRECTIONS

Shake well before use. Wet the hair coat with warm water and apply a sufficient amount of shampoo to create a rich lather. Massage shampoo into wet hair coat, lather freely. Rinse and repeat. Allow shampoo to remain on hair for 5 to 10 minutes, then rinse thoroughly with clean water. May be used initially 2 to 3 times a week for 4 weeks, then reducing to once a week, or as directed by your veterinarian.

CAUTIONS

If undue skin irritation develops or increases, discontinue use and consult a veterinarian.

STORAGE

Store at controlled room temperature.

Contains chlorhexidine & ketoconazole
Freshens & deodorizes
Treatment for dry, itchy irritated skin
Removes yeast, bacteria, fungus & ringworm

GENTLE ON SKIN
CHOSEN BY TOP VETS
FOR DOGS AND CATS

ALPHA PAW
Questions or Comments:
Call (800) 363-5458
www.alphapaw.com
Alpha Paw LLC, Las Vegas NV 89139

Packaging

Package 473mL